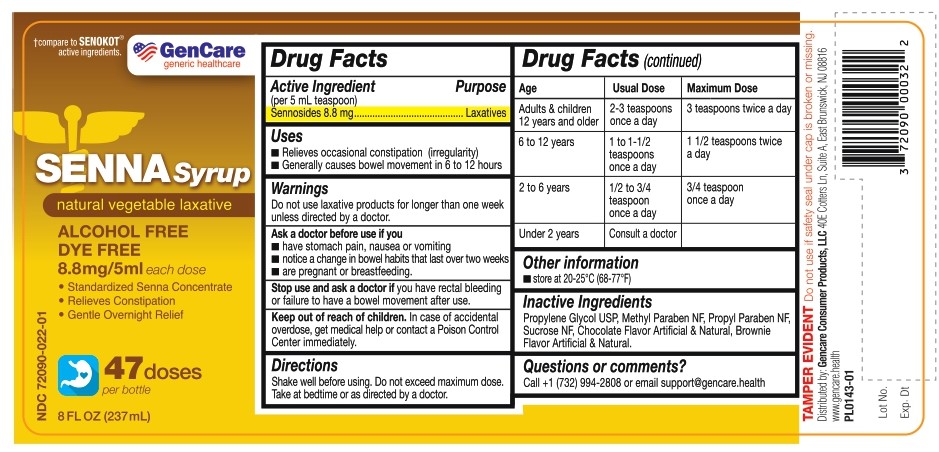 DRUG LABEL: Senna Syrup
NDC: 72090-022 | Form: SYRUP
Manufacturer: Pioneer Life Sciences, LLC
Category: otc | Type: HUMAN OTC DRUG LABEL
Date: 20251229

ACTIVE INGREDIENTS: SENNOSIDES 8.8 mg/5 mL
INACTIVE INGREDIENTS: PROPYLENE GLYCOL; METHYLPARABEN; PROPYLPARABEN; SUCROSE

Senna Syrup

Active Ingredient (per 5 mL teaspoon)

Sennosides 8.8 mg

Purpose

Laxative

Uses

- Relieves occasional constipation (irregularity)
- Generally causes bowel movement in 6 to 12 hours

Warnings

Do not use laxative products for longer than one week unless directed by a doctor.

Ask a doctor before use if you

- have stomach pain, nausea or vomiting
- notice a change in bowel habits that last over two weeks
- are pregnant or breastfeeding

Stop use and ask a doctor if

you have rectal bleeding or failure to have a bowel movement after use.

Keep out of reach of children.

In case of accidental overdose, get medical help or contact a Poison Control Center immediately.

Directions

Shake well before using. Do not exceed maximum dose. Take at bedtime or as directed by a doctor.

Age | Usual Dose | Maximum Dose
Adults & children 12 years and older | 2-3 teaspoons once a day | 3 teaspoons twice a day
6 to 12 years | 1 to 1-1/2 teaspoons once a day | 1 1/2 teaspoons twice a day
2 to 6 years | 1/2 to 3/4 teaspoon once a day | 3/4 teaspoon once a day
Under 2 years | Consult a doctor

Other Information

- store at 20-25°C (68-77°F)

Inactive Ingredients

Propylene Glycol USP, Methyl Paraben NF, Propyl Paraben NF, Sucrose NF, Chocolate Flavor Artificial & Natural, Brownie Flavor Artificial & Natural.

Questions or comments?

Call + 1 (732) 994-2808 or email support@gencare.health